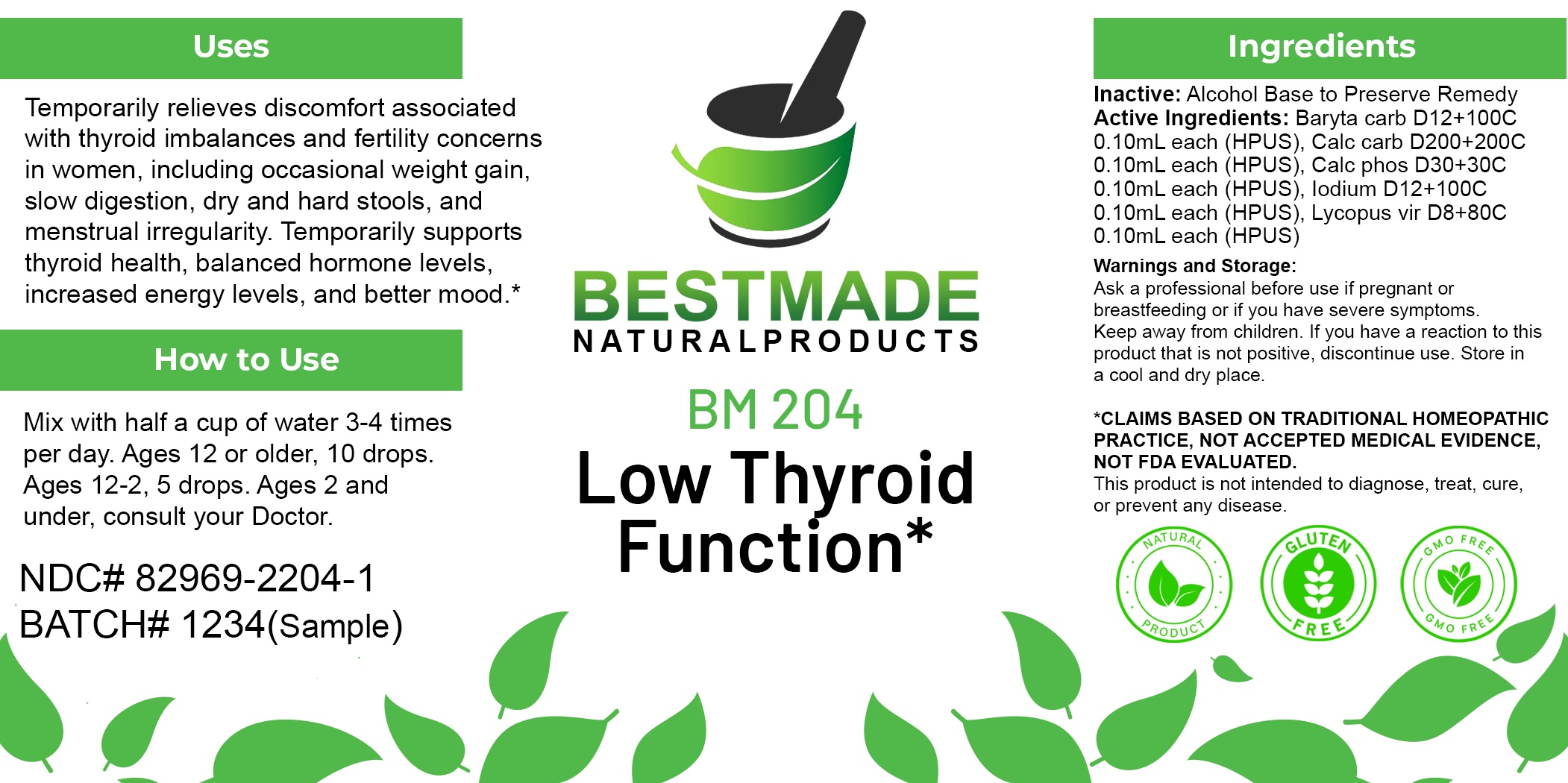 DRUG LABEL: Bestmade Natural Products BM204
NDC: 82969-2204 | Form: LIQUID
Manufacturer: Bestmade Natural Products
Category: homeopathic | Type: HUMAN OTC DRUG LABEL
Date: 20250226

ACTIVE INGREDIENTS: IODINE 30 [hp_C]/30 [hp_C]; BARIUM CARBONATE 30 [hp_C]/30 [hp_C]; LYCOPUS VIRGINICUS WHOLE 30 [hp_C]/30 [hp_C]; OYSTER SHELL CALCIUM CARBONATE, CRUDE 30 [hp_C]/30 [hp_C]; TRIBASIC CALCIUM PHOSPHATE 30 [hp_C]/30 [hp_C]
INACTIVE INGREDIENTS: ALCOHOL 30 [hp_C]/30 [hp_C]

BM204

DOSAGE AND ADMINISTRATION

How to Use

Mix with half a cup of water 3-4 times per day. Ages 12 or older, 10 drops. Ages 12-2, 5 drops. Ages 2 and under, consult your Doctor.

ACTIVE INGREDIENTS:

Baryta carb D12+100C 0.10mL each (HPUS), Calc carb D200+200C 0.10mL each (HPUS), Calc phos D30+30C 0.10mL each (HPUS), Iodium D12+100C 0.10mL each (HPUS), Lycopus vir D8+80C 0.10mL each (HPUS)

Inactive:

Alcohol Base to Preserve Product

KEEP OUT OF REACH OF CHILDREN

Warnings and Storage:

Ask a professional before use if pregnant or breastfeeding or if you have severe symptoms.

Keep away from children. If you have a reaction to this product that is not positive, discontinue use. Store in a cool and dry place

*CLAIMS BASED ON TRADITIONAL HOMEOPATHIC PRACTICE, NOT ACCEPTED MEDICAL EVIDENCE NOT FDA EVALUATED.
This product is not intended to diagnose, treat, cure, or prevent any disease.

Warnings and Storage:

Ask a professional before use if pregnant or breastfeeding or if you have severe symptoms.

Keep away from children. If you have a reaction to this product that is not positive, discontinue use. Store in a cool and dry place

*CLAIMS BASED ON TRADITIONAL HOMEOPATHIC PRACTICE, NOT ACCEPTED MEDICAL EVIDENCE NOT FDA EVALUATED.
This product is not intended to diagnose, treat, cure, or prevent any disease.

Uses
Temporarily relieves discomfort associated with thyroid imbalances and fertility concerns in women, including occasional weight gain,
slow digestion, dry and hard stools, and menstrual irregularity. Temporarily supports thyroid health, balanced hormone levels, increased energy levels, and better mood.*

Uses
Temporarily relieves discomfort associated with thyroid imbalances and fertility concerns in women, including occasional weight gain,
slow digestion, dry and hard stools, and menstrual irregularity. Temporarily supports thyroid health, balanced hormone levels, increased energy levels, and better mood.*

Entire package label